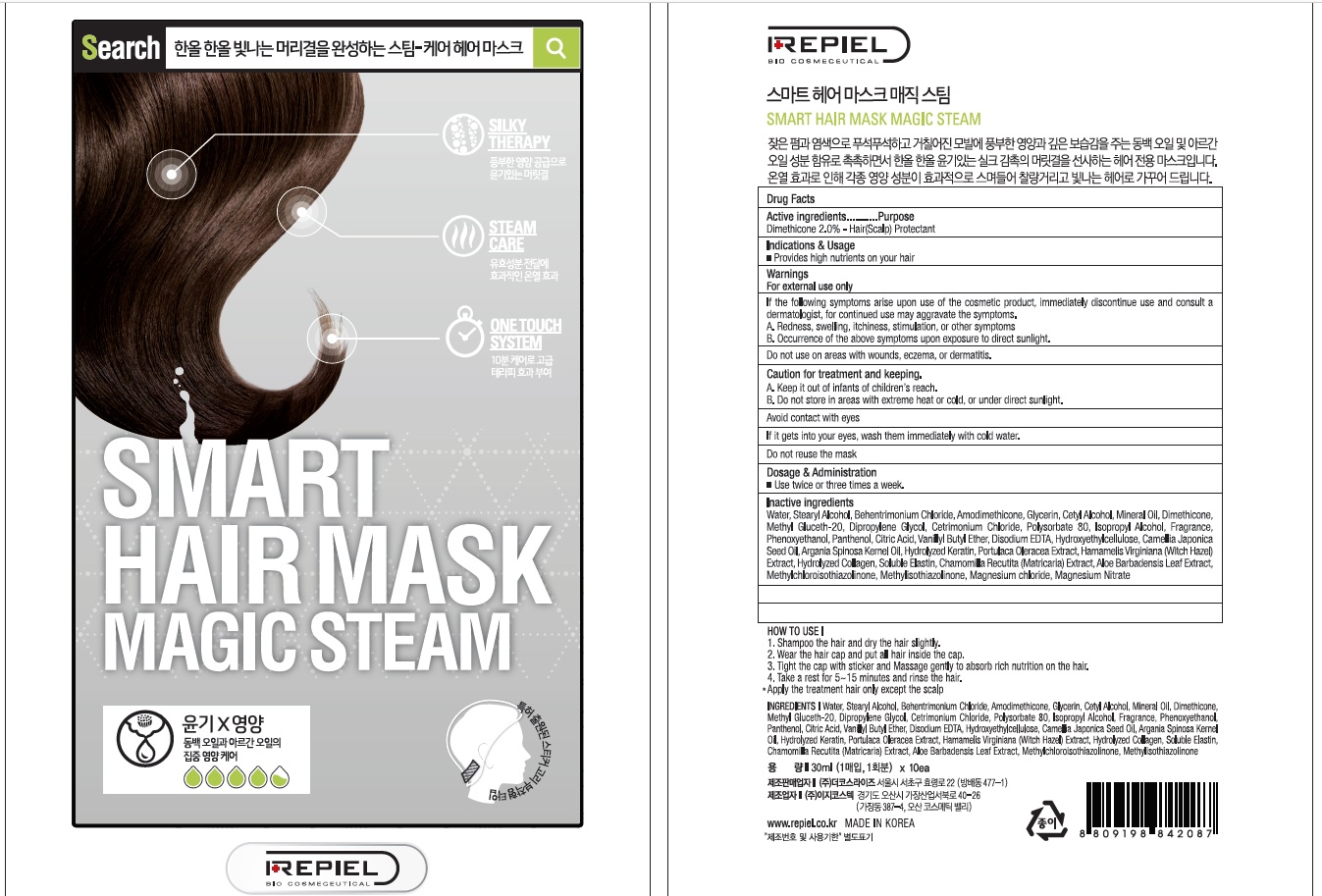 DRUG LABEL: REPIEL SMART HAIR MASK MAGIC STEAM
NDC: 70758-040 | Form: PATCH
Manufacturer: THE COSRISE CO.,LTD
Category: otc | Type: HUMAN OTC DRUG LABEL
Date: 20160629

ACTIVE INGREDIENTS: Dimethicone 0.6 g/30 mL
INACTIVE INGREDIENTS: Water; Glycerin

ACTIVE INGREDIENT

Active Ingredient: Dimethicone 2.0%

INACTIVE INGREDIENT

Inactive Ingredients: Water, Stearyl Alcohol, Behentrimonium Chloride, Amodimethicone, Glycerin, Cetyl Alcohol, Mineral Oil, Methyl Gluceth-20, Dipropylene Glycol, Cetrimonium Chloride, Polysorbate 80, Isopropyl Alcohol, Fragrance, Phenoxyethanol, Panthenol, Citric Acid, Vanillyl Butyl Ether, Disodium EDTA, Hydroxyethylcellulose, Camellia Japonica Seed Oil, Argania Spinosa Kernel Oil, Hydrolyzed Keratin, Portulaca Oleracea Extract, Hamamelis Virginiana (Witch Hazel) Extract, Hydrolyzed Collagen, Soluble Elastin, Chamomilla Recutita (Matricaria) Extract, Aloe Barbadensis Leaf Extract, Methylchloroisothiazolinone, Methylisothiazolinone, Magnesium chloride, Magnesium Nitrate

PURPOSE

Purpose: Hair(Scalp) Protectant

WARNINGS

Warnings: For external use only. 1. If the following symptoms arise upon use of the cosmetic product, immediately discontinue use and consult a dermatologist, for continued use may aggravate the symptoms. A. Redness, swelling, itchiness, stimulation, or other symptoms B. Occurrence of the above symptoms upon exposure to direct sunlight. 2. Do not use on areas with wounds, eczema, or dermatitis. 3. Caution for treatment and keeping. A. Keep it out of infants of children's reach. B. Do not store in areas with extreme heat or cold, or under direct sunlight. 4. Avoid the eye area 5. If it gets into your eyes, wash them immediately with cold water. 6. Do not reuse the mask

KEEP OUT OF REACH OF CHILDREN

Keep it out of infants of children's reach.

INDICATIONS & USAGE

Indications & Usage: Provides high nutrients on your hair

How to use: 1. Wash and cleanse the face to increase the effect of the mask 2. After removing mesh, apply the mask sheet smoothly to your face removing the fabric layer 3. Relax leaving the mask on, After 15~20 minute, peel away mask. Massage gently to maximize the effect of essence * Apply the treatment hair only except the scalp.

DOSAGE & ADMINISTRATION

Dosage & Administration: Use twice or three times a week.